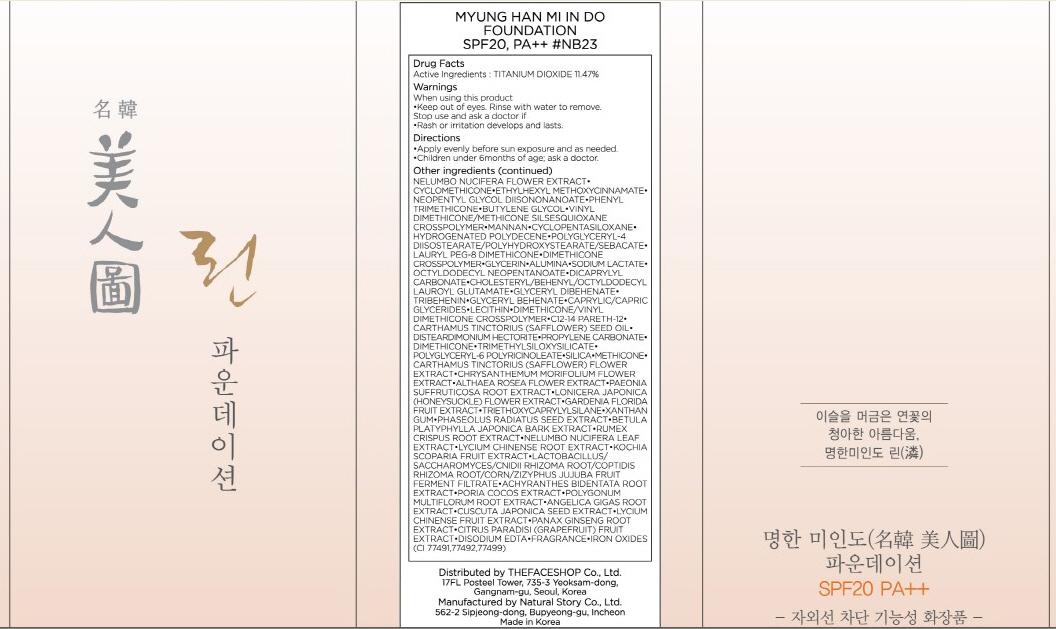 DRUG LABEL: MYUNG HAN MI IN DO FOUNDATION
NDC: 51523-014 | Form: CREAM
Manufacturer: THEFACESHOP CO., LTD.
Category: otc | Type: HUMAN OTC DRUG LABEL
Date: 20100714

ACTIVE INGREDIENTS: TITANIUM DIOXIDE 4.01 mL/35 mL

Drug Facts

Active Ingredient: TITANIUM DIOXIDE

Inactive Ingredients:
NELUMBO NUCIFERA FLOWER EXTRACT, CYCLOMETHICONE, ETHYLHEXYL METHOXYCINNAMATE, NEOPENTYL GLYCOL DIISONONANOATE, PHENYL TRIMETHICONE, BUTYLENE GLYCOL, VINYL DIMETHICONE/METHICONE SILSESQUIOXANE CROSSPOLYMER, MANNAN, CYCLOPENTASILOXANE, HYDROGENATED POLYDECENE, POLYGLYCERYL-4 DIISOSTEARATE/POLYHYDROXYSTEARATE/SEBACATE, LAURYL PEG-8 DIMETHICONE, DIMETHICONE CROSSPOLYMER, GLYCERIN, ALUMINA, SODIUM LACTATE, OCTYLDODECYL NEOPENTANOATE, DICAPRYLYL CARBONATE, CHOLESTERYL/BEHENYL/OCTYLDODECYL LAUROYL GLUTAMATE, GLYCERYL DIBEHENATE, TRIBEHENIN, GLYCERYL BEHENATE, CAPRYLIC/CAPRIC GLYCERIDES, LECITHIN, DIMETHICONE/VINYL DIMETHICONE CROSSPOLYMER, C12-14 PARETH-12, CARTHAMUS TINCTORIUS (SAFFLOWER) SEED OIL, DISTEARDIMONIUM HECTORITE, PROPYLENE CARBONATE, DIMETHICONE, TRIMETHYLSILOXYSILICATE, POLYGLYCERYL-6 POLYRICINOLEATE, SILICA, METHICONE, CARTHAMUS TINCTORIUS (SAFFLOWER) FLOWER EXTRACT, CHRYSANTHEMUM MORIFOLIUM FLOWER EXTRACT, ALTHAEA ROSEA FLOWER EXTRACT, PAEONIA SUFFRUTICOSA ROOT EXTRACT, LONICERA JAPONICA (HONEYSUCKLE) FLOWER EXTRACT, GARDENIA FLORIDA FRUIT EXTRACT, TRIETHOXYCAPRYLYLSILANE, XANTHAN GUM, PHASEOLUS RADIATUS SEED EXTRACT, BETULA PLATYPHYLLA JAPONICA BARK EXTRACT, RUMEX CRISPUS ROOT EXTRACT, NELUMBO NUCIFERA LEAF EXTRACT, LYCIUM CHINENSE ROOT EXTRACT, KOCHIA SCOPARIA FRUIT EXTRACT, LACTOBACILLUS/SACCHAROMYCES/CNIDII RHIZOMA ROOT/COPTIDIS RHIZOMA ROOT/CORN/ZIZYPHUS JUJUBA FRUIT FERMENT FILTRATE, ACHYRANTHES BIDENTATA ROOT EXTRACT, PORIA COCOS EXTRACT, POLYGONUM MULTIFLORUM ROOT EXTRACT, ANGELICA GIGAS ROOT EXTRACT, CUSCUTA JAPONICA SEED EXTRACT, LYCIUM CHINENSE FRUIT EXTRACT, PANAX GINSENG ROOT EXTRACT, CITRUS PARADISI (GRAPEFRUIT) FRUIT EXTRACT, DISODIUM EDTA, FRAGRANCE, IRON OXIDES(CI 77491,77492,77499)

Warnings:
When using this product
Keep out of eyes. Rinse with water to remove.
Stop use and ask a doctor if
Rash or irritation develops and lasts.
Directions:
Apply evenly before sun exposure and as needed.
Children under 6months of age; ask a doctor.